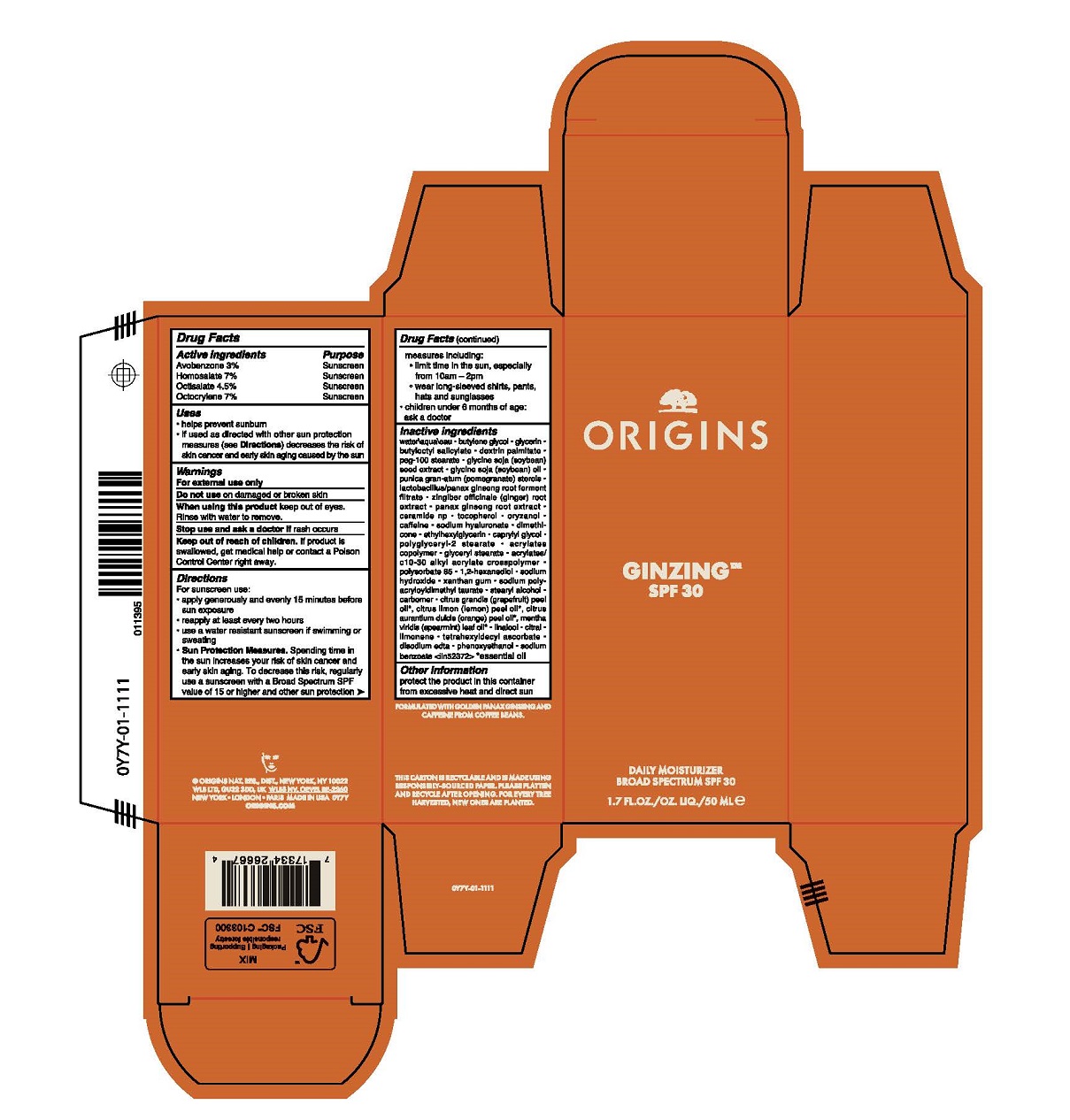 DRUG LABEL: GINZING SPF 30 DAILY MOISTURIZER
NDC: 59427-116 | Form: CREAM
Manufacturer: ORIGINS NATURAL RESOURCES INC.
Category: otc | Type: HUMAN OTC DRUG LABEL
Date: 20240103

ACTIVE INGREDIENTS: OCTOCRYLENE 70 mg/1 mL; AVOBENZONE 30 mg/1 mL; HOMOSALATE 70 mg/1 mL; OCTISALATE 45 mg/1 mL
INACTIVE INGREDIENTS: GLYCERIN; PEG-100 STEARATE; GINGER; ASIAN GINSENG; CERAMIDE NP; TOCOPHEROL; HYALURONATE SODIUM; DIMETHICONE; BUTYL ACRYLATE/METHYL METHACRYLATE/METHACRYLIC ACID COPOLYMER (18000 MW); ACRYLATES/C10-30 ALKYL ACRYLATE CROSSPOLYMER (60000 MPA.S); POLYSORBATE 85; 1,2-HEXANEDIOL; SODIUM HYDROXIDE; STEARYL ALCOHOL; CARBOXYPOLYMETHYLENE; SPEARMINT OIL; LINALOOL, (+/-)-; TETRAHEXYLDECYL ASCORBATE; PHENOXYETHANOL; SODIUM BENZOATE; PUNICA GRANATUM STEROLS; POLYGLYCERYL-2 STEARATE; XANTHAN GUM; SODIUM POLYACRYLOYLDIMETHYL TAURATE; CITRUS MAXIMA FRUIT RIND OIL; LEMON OIL; CITRAL; LIMONENE, (+)-; EDETATE DISODIUM ANHYDROUS; BUTYLOCTYL SALICYLATE; DEXTRIN PALMITATE (CORN; 20000 MW); SOYBEAN; WATER; ORYZANOL; ETHYLHEXYLGLYCERIN; CAPRYLYL GLYCOL; ORANGE OIL; SOYBEAN OIL; GLYCERYL MONOSTEARATE; BUTYLENE GLYCOL; CAFFEINE

GINZING SPF 30 DAILY MOISTURIZER

Active Ingredients

AVOBENZONE 3 %
HOMOSALATE 7%
OCTISALATE 4.5%
OCTOCRYLENE 7%

Purpose

Sunscreen

Uses

- helps prevent sunburn
- if used as directed with other sun protection measures (see Directions) decreases the risk of skin cancer and early skin aging caused by the sun

Warnings

For External use only

Do not use

on damaged or broken skin

When using this product

keep out of eyes. Rinse with water to remove.

Stop use and ask a doctor

if rash occurs

Keep out of reach of children.

If product is swallowed, get medical help or contact a Poison Control Center right away.

Directions

For sunscreen use:

- apply generously and evenly 15 minutes before sun exposure
- reapply at least every two hours
- use a water resistant sunscreen if swimming or sweating
- Sun Protection Measures. Spending time in the sun increases your risk of skin cancer and early skin aging. To decrease this risk, regularly use a sunscreen with a Broad Spectrum SPF value of 15 or higher and other sun protection measures including:
  - limit time in the sun, especially from 10 a.m.–2 p.m.
- wear long-sleeved shirts, pants, hats and sunglasses
- children under 6 months of age: ask a doctor

Inactive Ingredients

water\aqua\eau,butylene glycol,glycerin,butyloctyl salicylate,dextrin palmitate,peg-100 stearate,glycine soja (soybean) seed extract,glycine soja (soybean) oil,punica granatum (pomegranate) sterols,lactobacillus/panax ginseng root ferment filtrate,zingiber officinale (ginger) root extract,panax ginseng root extract,ceramide np,tocopherol,oryzanol,caffeine,sodium hyaluronate,dimethicone,ethylhexylglycerin,caprylyl glycol,polyglyceryl-2 stearate,acrylates copolymer,glyceryl stearate,acrylates/c10-30 alkyl acrylate crosspolymer,polysorbate 85,1,2-hexanediol,sodium hydroxide,xanthan gum,sodium polyacryloyldimethyl taurate,stearyl alcohol,carbomer,citrus grandis (grapefruit) peel oil*, citrus limon (lemon) peel oil*, citrus aurantium dulcis (orange) peel oil*, mentha viridis (spearmint) leaf oil*,linalool,citral,limonene,tetrahexyldecyl ascorbate,disodium edta,phenoxyethanol,sodium benzoate <iln52372>

Other Information

protect the product in this container from excessive heat and direct sun

Principal Display Panel

ORIGINS

GINZING SPF 30

DAILY MOISTURIZER

BROAD SPECTRUM SPF30

1.7 FL.OZ/OZ.LIQ./50 ML e